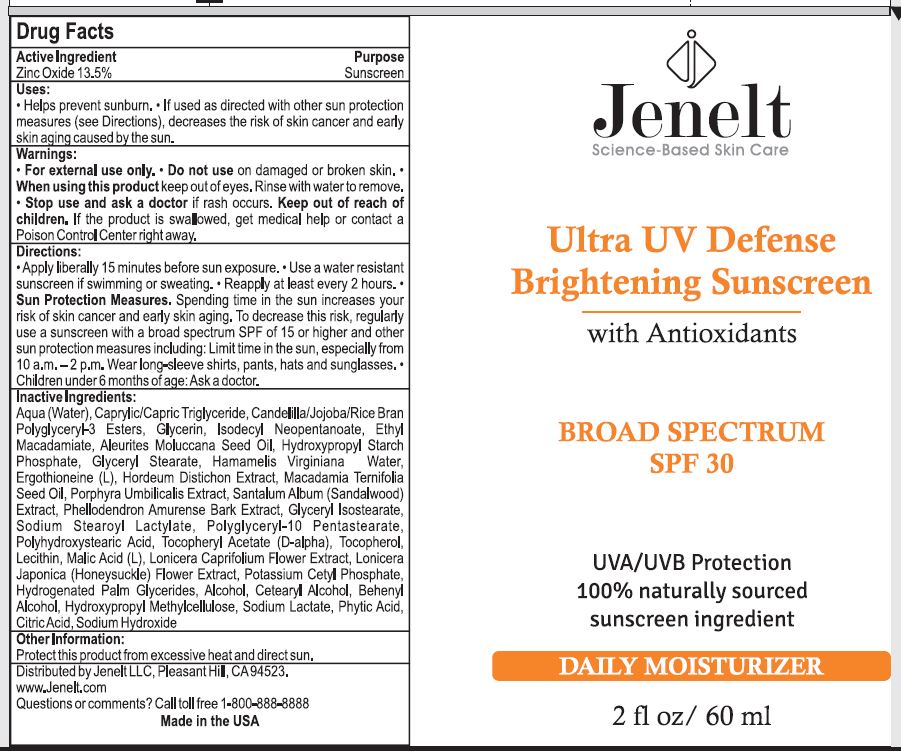 DRUG LABEL: Ultra UV Defense SPF 30
NDC: 58469-6100 | Form: CREAM
Manufacturer: Jenelt Cosmetics
Category: otc | Type: HUMAN OTC DRUG LABEL
Date: 20151111

ACTIVE INGREDIENTS: ZINC OXIDE 0.135 mg/1 g
INACTIVE INGREDIENTS: ISODECYL NEOPENTANOATE; ETHYL MACADAMIATE; KUKUI NUT OIL; HAMAMELIS VIRGINIANA LEAF WATER; ERGOTHIONEINE; WATER; MEDIUM-CHAIN TRIGLYCERIDES; GLYCERIN; BARLEY; MACADAMIA OIL; PORPHYRA UMBILICALIS; SANDALWOOD; PHELLODENDRON AMURENSE BARK; GLYCERYL ISOSTEARATE; SODIUM STEAROYL LACTYLATE; POLYGLYCERIN-10; POLYHYDROXYSTEARIC ACID (2300 MW); .ALPHA.-TOCOPHEROL ACETATE, D-; TOCOPHEROL; EGG PHOSPHOLIPIDS; MALIC ACID; LONICERA CAPRIFOLIUM FLOWER; LONICERA JAPONICA FLOWER; POTASSIUM CETYL PHOSPHATE; HYDROGENATED PALM GLYCERIDES; ALCOHOL; CETOSTEARYL ALCOHOL; DOCOSANOL; HYPROMELLOSE 2208 (100 MPA.S); SODIUM LACTATE; PHYTIC ACID; CITRIC ACID MONOHYDRATE; SODIUM HYDROXIDE

Drug Facts OTC #610; Ultra UV Defense SPF 30

Active Ingredient:

Zinc Oxide 13.5%

Purpose: Sunscreen

Keep out of reach of children. If the product is swallowed, get medical help or contact a Poison Control Center right away.

Uses:

- Helps prevent sunburn.
- If used as directed with other sun protection measures (see Directions), decreases the risk of skin cancer and early skin aging caused by the sun.

Warnings:

- For external use only.
- Do not use on damaged or broken skin.
- When using this product keep out of eyes. Rinse with water to remove.
- Stop use and ask a doctor if rash occurs.
- Keep out of reach of children. If the product is swallowed, get medical help or contact a Poison Control Center right away.

Directions:

- Apply liberally 15 minutes before sun exposure.
- Use a water resistant sunscreen if swimming or sweating.
- Reapply at least every 2 hours.
- Sun Protection Measures. Spending time in the sun increases your risk of skin cancer and early skin aging. To decrease this risk, regularly use a sunscreen with a broad spectrum SPF of 15 or higher and other sun protection measures including: Limit time in the sun, especially from 10 a.m. - 2 p.m. Wear long-sleeve shirts, pants, hats and sunglasses.
- Children under 6 months: Ask a doctor.

INACTIVE INGREDIENT

Inactive Ingredients: Aqua (Water), Caprylic/Capric Triglyceride, Candelilla/Jojoba/Rice Bran Polyglyceryl-3 Esters, Glycerin, Isodecyl Neopentanoate, Ethyl Macadamiate, Aleurites Moluccana Seed Oil, Hydroxypropyl Starch Phosphate, Glyceral Stearate, Hamamelis Virginiana (Witch Hazel) Water, Ergothioneine (L), Hordeum Distichon (Barley) Extract, Macadamia Ternifolia Seed Oil, Porphyra Umbilicalis (Red Algae) Extract, Santalum Album (Sandalwood) Extract, Phellodendron Amurense Bark Extract, Glyceryl Isostearate, Sodium Stearoyl Lactylate, Polyglyceryl-10 Pentastearate, Polyhydroxystearic Acid, Tocopheryl Acetate (D-alpha), Tocopherol (D-alpha), Lecithin, Malic Acid (L) Lonicera Caprifolium (Honeysuckle) Flower Extract, Lonicera Japonica (Honeysuckle) Flower Extract, Potassium Cetyl Phosphate, Hydrogenated Palm Glycerides, Alcohol, Cetearyl Alcohol, Behenyl Alchohol, Hydroxypropyl Methylcellulose, Sodium Lactate, Phytic Acid, Citric Acid, Sodium Hydroxide

Other Information:

- Protect this product from excessive heat and direct sun.